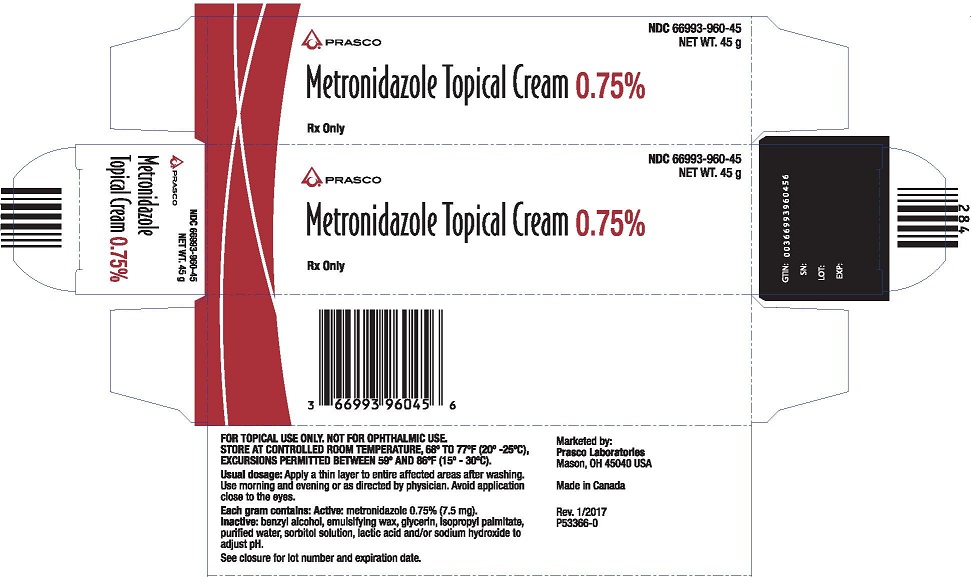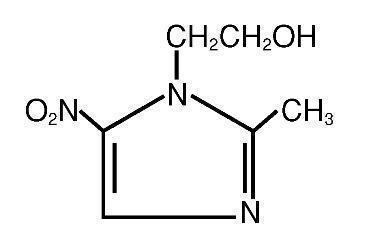 DRUG LABEL: METRONIDAZOLE
NDC: 66993-960 | Form: CREAM
Manufacturer: Prasco Laboratories
Category: prescription | Type: HUMAN PRESCRIPTION DRUG LABEL
Date: 20241107

ACTIVE INGREDIENTS: METRONIDAZOLE 7.5 mg/1 g
INACTIVE INGREDIENTS: BENZYL ALCOHOL; GLYCERIN; ISOPROPYL PALMITATE; WATER; SORBITOL; LACTIC ACID; SODIUM HYDROXIDE

Metronidazole
Topical Cream, 0.75%
Rx only
FOR TOPICAL USE ONLY
(NOT FOR OPHTHALMIC USE)

DESCRIPTION:

Metronidazole Topical Cream contains metronidazole, USP, at a concentration of 7.5 mg per gram (0.75%) in an emollient cream consisting of benzyl alcohol, emulsifying wax, glycerin, isopropyl palmitate, purified water, sorbitol solution, lactic acid and/or sodium hydroxide to adjust pH. Metronidazole is a member of the imidazole class of antibacterial agents and is classified therapeutically as an antiprotozoal and antibacterial agent. Chemically, metronidazole is 2-methyl-5-nitro-1H- imidazole-1-ethanol. The molecular formula is C6H9N3O3 and molecular weight is 171.16. Metronidazole is represented by the following structural formula:

CLINICAL PHARMACOLOGY:

The mechanisms by which metronidazole acts in the treatment of rosacea are unknown, but appear to include an anti-inflammatory effect.

INDICATIONS AND USAGE:

Metronidazole Topical Cream is indicated for topical application in the treatment of inflammatory papules and pustules of rosacea.

CONTRAINDICATIONS:

Metronidazole Topical Cream is contraindicated in individuals with a history of hypersensitivity to metronidazole, or other ingredients of the formulation.

PRECAUTIONS:

General:

Topical metronidazole has been reported to cause tearing of the eyes. Therefore, contact with the eyes should be avoided. If a reaction suggesting local irritation occurs, patients should be directed to use the medication less frequently or discontinue use. Metronidazole is a nitroimidazole and should be used with care in patients with evidence of, or history of blood dyscrasia.

Information for patients:

This medication is to be used as directed by the physician. It is for external use only. Avoid contact with the eyes.

Drug Interactions:

Oral metronidazole has been reported to potentiate the anticoagulant effect of warfarin and coumarin anticoagulants, resulting in a prolongation of prothrombin time. The effect of topical metronidazole on prothrombin time is not known.

Carcinogenesis, mutagenesis, impairment of fertility:

Metronidazole has shown evidence of carcinogenic activity in a number of studies involving chronic, oral administration in mice and rats but not in studies involving hamsters.

Metronidazole has shown evidence of mutagenic activity in several in vitro bacterial assay systems. In addition, a dose-response increase in the frequency of micronuclei was observed in mice after intraperitoneal injections and an increase in chromosome aberrations have been reported in patients with Crohn's disease who were treated with 200-1200 mg/day of metronidazole for 1 to 24 months. However, no excess chromosomal aberrations in circulating human lymphocytes have been observed in patients treated for 8 months.

Pregnancy:

Teratogenic effects: Pregnancy category B: There are no adequate and well-controlled studies with the use of Metronidazole Topical Cream in pregnant women. Metronidazole crosses the placental barrier and enters the fetal circulation rapidly. No fetotoxicity was observed after oral metronidazole in rats or mice. However, because animal reproduction studies are not always predictive of human response and since oral metronidazole has been shown to be a carcinogen in some rodents, this drug should be used during pregnancy only if clearly needed.

Nursing mothers:

After oral administration, metronidazole is secreted in breast milk in concentrations similar to those found in the plasma. Even though blood levels are significantly lower with topically applied metronidazole than those achieved after oral administration of metronidazole, a decision should be made whether to discontinue nursing or to discontinue the drug, taking into account the importance of the drug to the mother.

Pediatric use:

Safety and effectiveness in pediatric patients have not been established.

ADVERSE REACTIONS:

In controlled clinical trials, the total incidence of adverse reactions associated with the use of Metronidazole Topical Cream was approximately 10%. Skin discomfort (burning and stinging) was the most frequently reported event followed by erythema, skin irritation, pruritus and worsening of rosacea. All individual events occurred in less than 3% of patients. The following additional adverse experiences have been reported with the topical use of metronidazole: dryness, transient redness, metallic taste, tingling or numbness of extremities and nausea.

DOSAGE AND ADMINISTRATION:

Apply and rub in a thin layer of Metronidazole Topical Cream twice daily, morning and evening, to entire affected areas after washing. Areas to be treated should be washed with a mild cleanser before application. Patients may use cosmetics after application of Metronidazole Topical Cream.

HOW SUPPLIED:

Metronidazole Topical Cream, 0.75% is supplied in a 45 g aluminum tube - NDC 66993-960-45.

Storage conditions: STORE AT CONTROLLED ROOM TEMPERATURE, 68° TO 77°F (20° TO 25°C), EXCURSIONS PERMITTED BETWEEN 59° TO 86°F (15° TO 30°C).

Marketed by:
Prasco Laboratories
Mason, OH 45040 USA
Made in Canada

P53365-0
Issued: March 2017

Package Label

PRASCO NDC 66993-960-45

NET WT. 45 g

Metronidazole Topical Cream 0.75%

Rx Only

FOR TOPICAL USE ONLY. NOT FOR OPHTHALMIC USE.

STORE AT CONTROLLED ROOM TEMPERATURE, 68° TO 77°F (20° TO 25°C), EXCURSIONS PERMITTED BETWEEN 59° TO 86°F (15° TO 30°C).

Usual dosage: Apply a thin layer to entire affected areas after washing. Use morning and evening or as directed by physician. Avoid application close to the eyes.

Each gram contains: Active: metronidazole 0.75% (7.5 mg).

Inactive: benzyl alcohol, emulsifying wax, glycerin, isopropyl palmitate, purified water, sorbitol solution, lactic acid and/or sodium hydroxide to adjust pH.

See closure for lot number and expiration date.

Marketed by:

Prasco Laboratories

Mason, OH 45040 USA

Made in Canada

Rev. 1/2017

P53366-0